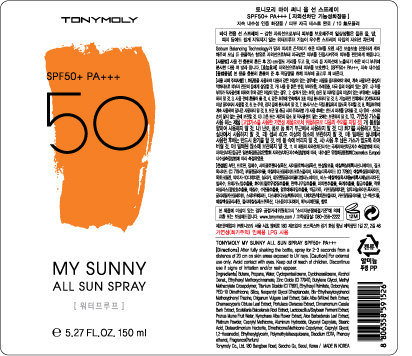 DRUG LABEL: TONYMOLY My Sunny All SunSpray
NDC: 59078-120 | Form: SPRAY
Manufacturer: Tonymoly Co., Ltd.
Category: otc | Type: HUMAN OTC DRUG LABEL
Date: 20160204

ACTIVE INGREDIENTS: TITANIUM DIOXIDE 20557.8 mg/150 mL; OCTOCRYLENE 4725 mg/150 mL
INACTIVE INGREDIENTS: BEMOTRIZINOL; CAPRYLYL TRISILOXANE; EDETATE DISODIUM; ALOE VERA LEAF; PORTULACA OLERACEA WHOLE; CHINESE CINNAMON; NYMPHAEA ALBA FLOWER; OREGANO; WILLOW BARK; PLATINUM; NEOPENTYL GLYCOL DIHEPTANOATE; GLYCERYL CAPRYLATE; BUTYLENE GLYCOL; ETHYLHEXYL PALMITATE; STEARIC ACID; ALUMINUM HYDROXIDE; DISTEARDIMONIUM HECTORITE; CAPRYLYL GLYCOL; WATER; PHENOXYETHANOL; 1,2-HEXANEDIOL; ETHYLHEXYLGLYCERIN; CYCLOMETHICONE 5; ALCOHOL; PRUNUS MUME FRUIT; CHAMAECYPARIS OBTUSA LEAF; SCUTELLARIA BAICALENSIS ROOT

Active Ingredients

Ethylhexyl Methoxycinnamate 7.30%, Octocrylene 3.00%, Titanium Dioxide 3.24%, Zinc Oxide 4.32%

Purpose

Skin Protectant

Use

Sunscreen

Caution

For external use only. Avoid contact with eyes. Keep out of reach of children. Discontinue use if signs of irritation and/or rash appear.

Keep out of reach of children

Directions

After fully shaking the bottle, spray for 2-3 seconds from a distance of 20 cm on skin areas exposed to UV rays.

Inactive Ingredients

Water, Cyclopentasiloxane, Cyclohexasiloxane, Alcohol Denat., Butylene Glycol, Methyl Methacrylate Crosspolymer, Ethylhexyl Palmitate, PEG-10 Dimethicone, Silica, Neopentyl Glycol Diheptanoate, Bis-Ethylhexyloxyphenol Methoxyphenyl Triazine, Caprylyl Methicone, Aluminum Hydroxide, Glyceryl Caprylate, Stearic Acid, Disteardimonium Hectorite, Fragrance(Parfum), Dimethicone/Methicone Copolymer, Caprylyl Glycol, Disodium EDTA, Water, Phenoxyethanol, Prunus Mume Fruit Water, Nymphaea Alba Flower Extract, Aloe Barbadensis Leaf Extract, 1,2-Hexanediol, Origanum Vulgare Leaf Extract, Salix Alba (Willow) Bark Extract, Chamaecyparis Obtusa Leaf Extract, Ethylhexylglycerin, Portulaca Oleracea Extract, Cinnamomum Cassia Bark Extract, Scutellaria Baicalensis Root Extract, Lactobacillus/Soybean Ferment Extract, Polymethylsilsesquioxane, Platinum Powder